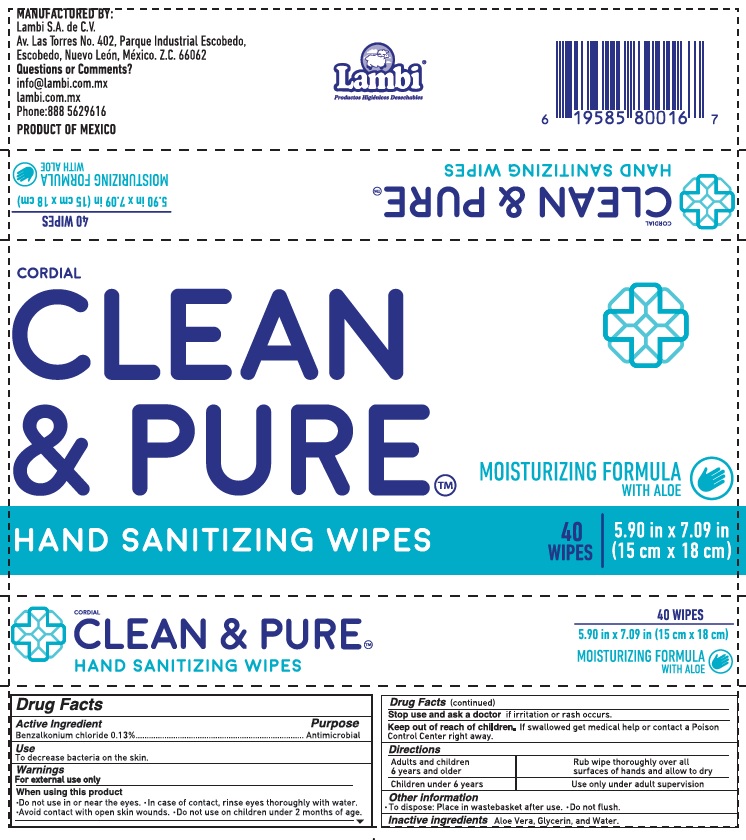 DRUG LABEL: Cordial Clean and Pure
NDC: 81510-001 | Form: CLOTH
Manufacturer: Lambi, S.A. de C.V.
Category: otc | Type: HUMAN OTC DRUG LABEL
Date: 20210426

ACTIVE INGREDIENTS: BENZALKONIUM CHLORIDE 0.13 g/100 g
INACTIVE INGREDIENTS: GLYCERIN; ALOE VERA LEAF; WATER

Wipes: 40

Active Ingredient

Benzalkonium chloride 0.13% v/v. Purpose: Antimicrobial

Purpose

Antimicrobial

Use

To decrease bacteria on the skin.

Warnings

For external use only. Flammable.

When using this product

*Do nor use in or near the eyes.

*In case of contact, rinse eyes thoroughly with water.
*Avoid contact with open skin wouds.

*Do not use on children under 2 months of age.

Stop use and ask a doctor

if irritation or rash occurs.

Keep out of reach of children

If swallowed get medical help or contact a Poison Control Center right away.

Directions

- Adults and children 6 years and older: Rub wipe thoroughly over all surfaces of hands and allow to dry.
- Children under 6 years: Use only under adult supervision.

Other information

- To dispose: Place in wastebasket after use.
- Do not flush.

Inactive ingredients

Aloe Vera, Glycerin, and Water.

Package Label - Principal Display Panel

40 wipes NDC: 81510-001-01